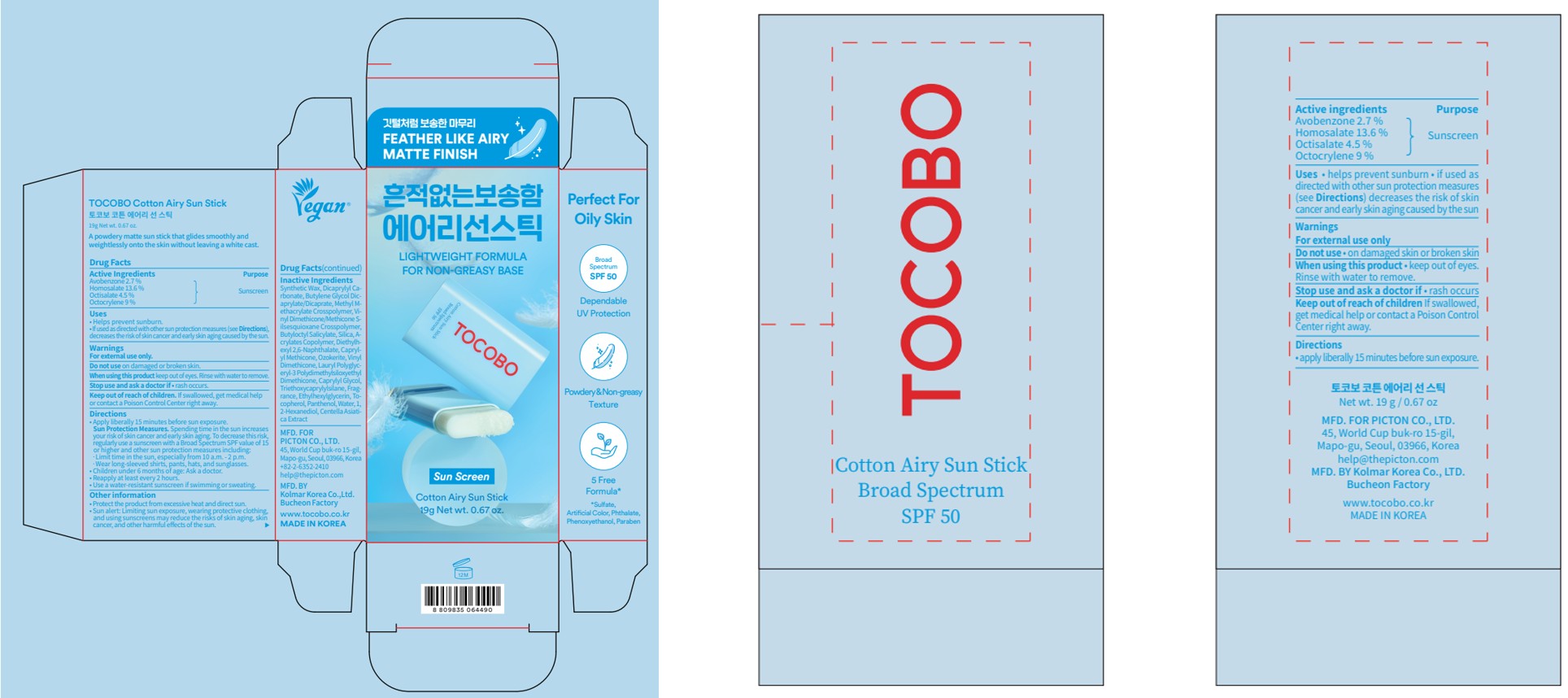 DRUG LABEL: TOCOBO Cotton Airy Sun Stick
NDC: 85287-119 | Form: STICK
Manufacturer: PICTON CO., Ltd.
Category: otc | Type: HUMAN OTC DRUG LABEL
Date: 20251014

ACTIVE INGREDIENTS: HOMOSALATE 2.584 g/19 g; OCTOCRYLENE 1.71 g/19 g; OCTISALATE 0.855 g/19 g; AVOBENZONE 0.513 g/19 g
INACTIVE INGREDIENTS: CAPRYLYL METHICONE; CAPRYLYL GLYCOL; VINYL DIMETHICONE/METHICONE SILSESQUIOXANE CROSSPOLYMER; CENTELLA ASIATICA TRITERPENOIDS; DIETHYLHEXYL 2,6-NAPHTHALATE; SILICA; WATER; DICAPRYLYL CARBONATE; TOCOPHEROL; PANTHENOL; TRIETHOXYCAPRYLYLSILANE; ETHYLHEXYLGLYCERIN; 1,2-HEXANEDIOL; BUTYLENE GLYCOL DICAPRYLATE/DICAPRATE

TOCOBO Cotton Airy Sun Stick 19g

Active Ingredients

Avobenzone 2.7 %

Homosalate 13.6 %

Octisalate 4.5 %

Octocrylene 9 %

Purpose

Sunscreen

Uses

• Helps prevent sunburn
• If used as directed with other sun protection measures (see Directions), decreases the risk of skin cancer and early skin aging caused by the sun

Warnings

For external use only

Do not use

on damaged or broken skin

When using this product

keep out of eyes. Rinse with water to remove.

Stop use and ask a doctor

if rash occurs

Keep out of reach of children.

If swallowed, get medical help or contact a Poison Control Center right away.

Directions

• apply liberally 15 minutes before sun exposure.
Sun Protection Measures.Spending time in the sun increases your risk of skin cancer and early skin aging. To decrease this risk,
regularly use a sunscreen with a Broad Spectrum SPF value of 15 or higher and other sun protection measures including:
·limit time in the sun, especially from 10 a.m. - 2 p.m.
·wear long-sleeved shirts, pants, hats, and sunglasses
• children under 6 months of age: Ask a doctor
• reapply at least every 2 hours
• use a water-resistant sunscreen if swimming or sweating

Other information

• protect the product from excessive heat and direct sun
• Sun alert: Limiting sun exposure, wearing protective clothing, and using sunscreens may reduce the risks of skin aging, skin cancer, and other harmful eﬀects of the sun.

Inactive Ingredients

Synthetic Wax, Dicaprylyl Carbonate, Butylene Glycol Dicaprylate/Dicaprate, Methyl Methacrylate Crosspolymer, Vinyl Dimethicone/Methicone Silsesquioxane Crosspolymer, Butyloctyl Salicylate, Silica, Acrylates Copolymer, Diethylhexyl 2,6-Naphthalate, Caprylyl Methicone, Ozokerite, Vinyl Dimethicone, Lauryl Polyglyceryl-3 Polydimethylsiloxyethyl Dimethicone, Caprylyl Glycol, Triethoxycaprylylsilane, Fragrance, Ethylhexylglycerin, Tocopherol, Panthenol, Water, 1,2-Hexanediol, Centella Asiatica Extract